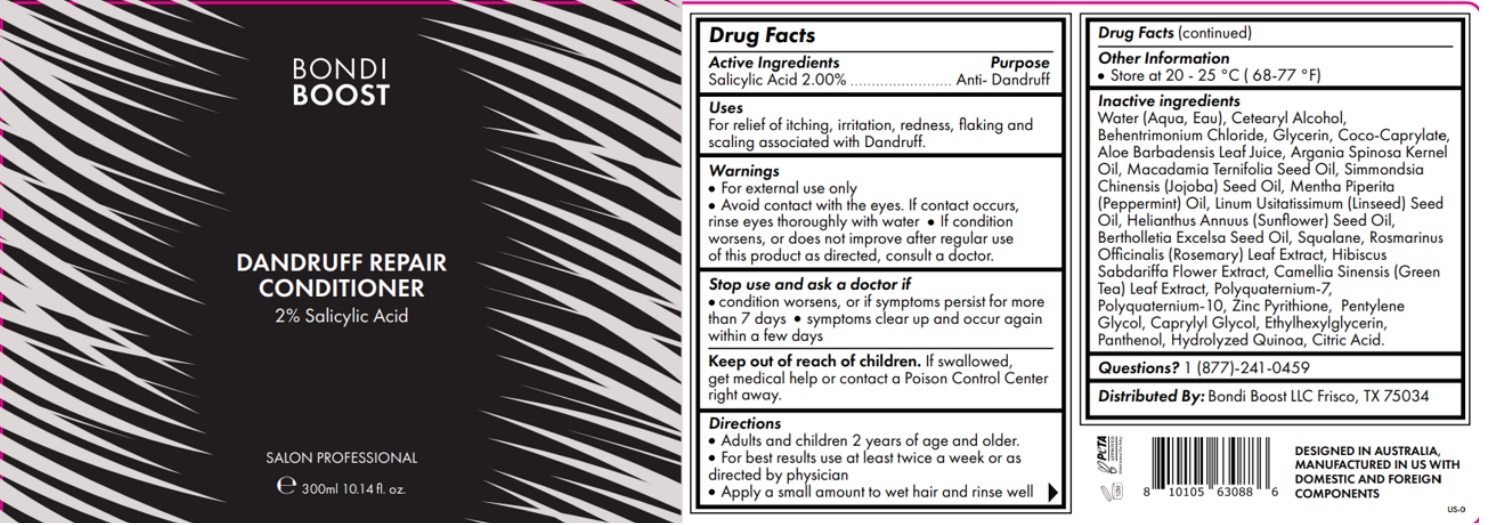 DRUG LABEL: Conditioner
NDC: 84169-002 | Form: LOTION
Manufacturer: Bondi Boost U.s LLC
Category: otc | Type: HUMAN OTC DRUG LABEL
Date: 20241223

ACTIVE INGREDIENTS: SALICYLIC ACID 2 g/100 mL
INACTIVE INGREDIENTS: ARGAN OIL; COCO-CAPRYLATE; BEHENTRIMONIUM CHLORIDE; CETOSTEARYL ALCOHOL; POLYQUATERNIUM-10 (400 MPA.S AT 2%); ROSEMARY; HIBISCUS SABDARIFFA FLOWER; GREEN TEA LEAF; POLYQUATERNIUM-7 (70/30 ACRYLAMIDE/DADMAC; 1600 KD); PYRITHIONE ZINC; BRAZIL NUT OIL; SUNFLOWER OIL; PANTHENOL; MENTHA PIPERITA; CITRIC ACID MONOHYDRATE; ALOE VERA LEAF; WATER; CAPRYLYL GLYCOL; ETHYLHEXYLGLYCERIN; SQUALENE; SIMMONDSIA CHINENSIS SEED; LINSEED OIL; GLYCERIN; PENTYLENE GLYCOL; MACADAMIA OIL; CHENOPODIUM QUINOA SEED

Bondi Boost Dandruff Repair Conditioner

Drug Facts

Active Ingredients | Purpose
Salicylic Acid 2.00% | Anti - Dandruff

Stop use and ask a doctor if

- Condition worsens, or if Symptoms persist for mre than 7 days
- symptoms clear up and occur again witin a few days

Keep Out of reach of children: If swallowed, get medical help or contact a Posion Control Center right away.

Questions?

Questions? 1 (877)-241-0459

Warnings

- For external use only
- Avoid contact with eyes. If contact occurs, rinse eyes thoroughly with water
- If condition worsens, or does not improve after regular use of this product as directed, consult a doctor.

STORAGE AND HANDLING

Store at 20 -25 °C (68- 77 ° F)

Inactive ingredients

Water (Aqua, Eau), Cetearyl alcohol, Behentrimonium Chloride,Glycerin, Coco-Caprylate,Aloe Barbadensis Leaf Juice, Argania Spinosa Kernal Oil, Macadamia Ternifolia Seed Oil, Simmondsia Chinesis (Jojoba) Seed Oil, Mentha Piperita (Peppermint) Oil, Linum Usitatissimum (Linseed) Seed Oil, Helianthus Annuus (Sunflower) Seed Oil, Bertholletia Excelsa Seed Oil, Squalene, Rosmarinus Officinalis (Rosemary) Leaf Extract, Hibiscus Sabdariffa Flower Extract, Camellia Sinesis (Green Tea) Leaf Extract, Polyquaternium-7, Polyquaternium-10, Zinc Pyrithione, Pentylene Glycol, Caprylyl Glycol, Ethylhexylglycerin, Panthenol, Hydrolyzed Quinoa, Citric Acid

INDICATIONS AND USAGE

For Relief of itching, irritation, redness, flaking and scaling associated with Dandruff.

Directions:

Adults and children 2 years of age and older

For best results use at least twice a week or as directed by physician

Apply a small amount to wet hair, lather and rinse well